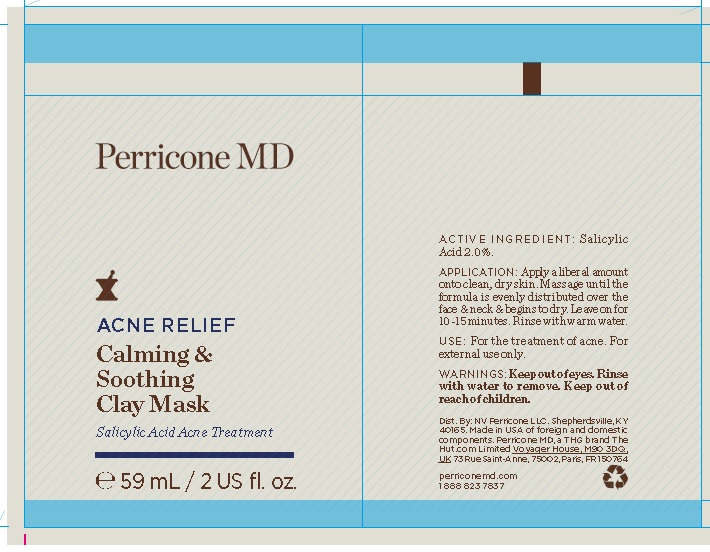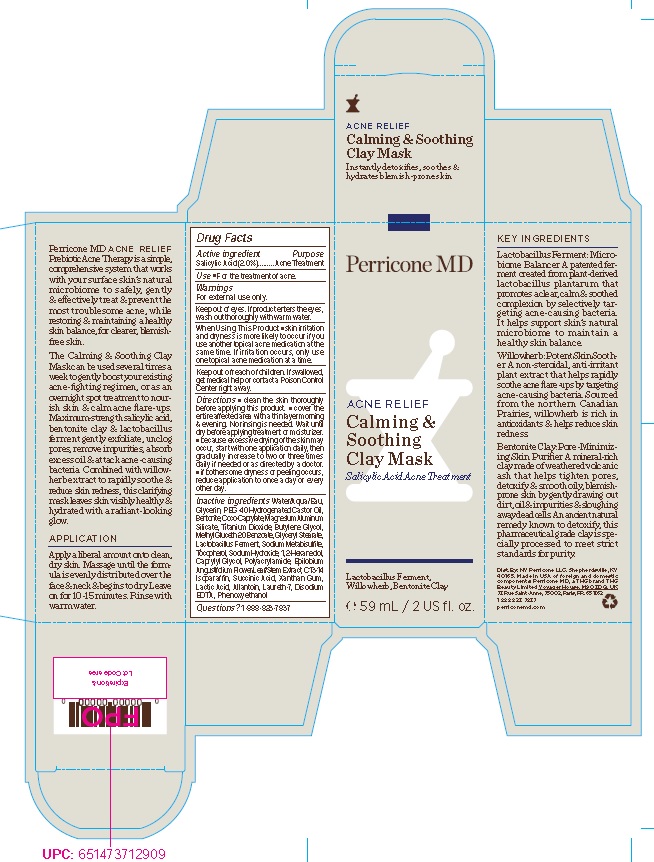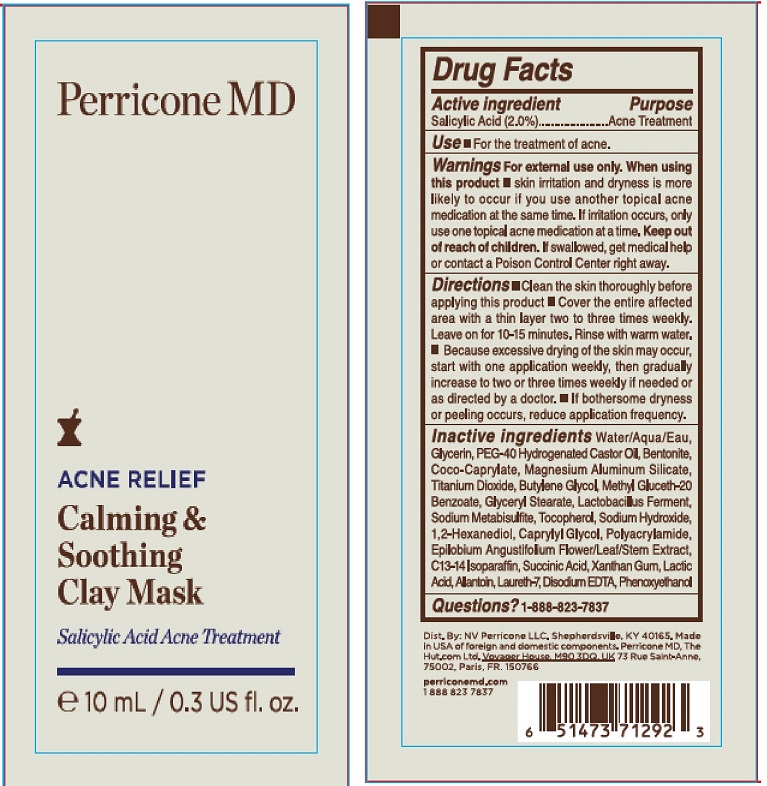 DRUG LABEL: Perricone Acne Relief Calming and Soothing Clay Mask
NDC: 54111-156 | Form: LOTION
Manufacturer: Bentley Laboratories, LLC
Category: otc | Type: HUMAN OTC DRUG LABEL
Date: 20211004

ACTIVE INGREDIENTS: SALICYLIC ACID 2.0 g/100 mL
INACTIVE INGREDIENTS: WATER; GLYCERIN; POLYOXYL 40 HYDROGENATED CASTOR OIL; BENTONITE; COCO-CAPRYLATE; MAGNESIUM ALUMINUM SILICATE; TITANIUM DIOXIDE; BUTYLENE GLYCOL; METHYL GLUCETH-20; BENZOIC ACID; GLYCERYL MONOSTEARATE; LACTOBACILLUS FERMENTUM; SODIUM METABISULFITE; TOCOPHEROL; SODIUM HYDROXIDE; 1,2-HEXANEDIOL; CAPRYLYL GLYCOL; POLYACRYLAMIDE (10000 MW); EPILOBIUM ANGUSTIFOLIUM FLOWERING TOP; C13-14 ISOPARAFFIN; SUCCINIC ACID; XANTHAN GUM; LACTIC ACID; ALLANTOIN; LAURETH-7; EDETATE DISODIUM ANHYDROUS; PHENOXYETHANOL

Perricone MD Acne Relief Calming and Soothing Clay Mask

Drug Facts

Active Ingredient

Salicylic Acid (2.0%)

Purpose
Acne Treatment

INDICATIONS AND USAGE

Use ■ For the treatment of acne.

Warnings
For external use only.

Keep out of eyes. If product enters the eyes,
wash out thoroughly with warm water.

When Using This Product ■ skin irritation
and dryness is more likely to occur if you
use another topical acne medication at the
same time. If irritation occurs, only use
one topical acne medication at a time.

Keep out of reach of children. If swallowed,
get medical help or contact a Poison Control
Center right away.

DOSAGE AND ADMINISTRATION

Directions ■ clean the skin thoroughly
before applying this product. ■ cover the
entire affected area with a thin layer morning
& evening. No rinsing is needed. Wait until
dry before applying treatment or moisturizer.
■ because excessive drying of the skin may
occur, start with one application daily, then
gradually increase to two or three times
daily if needed or as directed by a doctor.
■ if bothersome dryness or peeling occurs,
reduce application to once a day or every
other day.

Inactive ingredients Water/Aqua/Eau,
Glycerin, PEG-40 Hydrogenated Castor Oil,
Bentonite, Coco-Caprylate, Magnesium Aluminum
Silicate, Titanium Dioxide, Butylene Glycol,
Methyl Gluceth-20 Benzoate, Glyceryl Stearate,
Lactobacillus Ferment, Sodium Metabisulfite,
Tocopherol, Sodium Hydroxide, 1,2-Hexanediol,
Caprylyl Glycol, Polyacrylamide, Epilobium
Angustifolium Flower/Leaf/Stem Extract, C13-14
Isoparaffin, Succinic Acid, Xanthan Gum,
Lactic Acid, Allantoin, Laureth-7, Disodium
EDTA, Phenoxyethanol

Questions?1-888-823-7837

Product Label

Perricone MD

ACNE RELIEF

Calming &
Soothing
Clay Mask
Salicylic Acid Acne Treatment

Lactobacillus Ferment,
Willowherb, Bentonite Clay

℮ 59 mL / 2 US fl. oz.

Dist. By: NV Perricone LLC. Shepherdsville, KY
40165. Made in USA of foreign and domestic
components. Perricone MD, a THG brand THG
Beauty Limited Voyager House, M90 3DQ, UK
73 Rue Saint-Anne, 75002, Paris, FR. 651362
1 888 823 7837
perriconemd.com

59 nL Carton

10 mL Packet

res